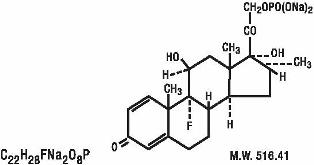 DRUG LABEL: Unknown
Manufacturer: Alcon
Category: prescription | Type: Human Prescription Drug Label
Date: 20061226

DESCRIPTION

MAXIDEX®(Dexamethasone Sodium Phosphate) is an adrenocortical steroid prepared as a sterile ophthalmic ointment. The active ingredient is represented by the chemical structure:

Established name:

Dexamethasone Sodium Phosphate

Chemical name:

Pregn-4-ene-3,20-dione,9-fluoro-11,17-dihydroxy-16-methyl-21-(phosphonoxy)-, disodium salt, (11β,16α)-.

Each gram contains: Active: Dexamethasone Sodium Phosphate equivalent to Dexamethasone Phosphate 0.5 mg (0.05%) Inactive: Mineral Oil.

White Petrolatum. DM-00

CLINICAL PHARMACOLOGY

Dexamethasone sodium phosphate suppresses the inflammatory response to a variety of agents and it probably delays or slows healing. No generally accepted explanation of these steroid properties has been advanced.

INDCIATIONS AND USAGE

Steroid responsive inflammatory conditions of the palpebral and bulbar conjunctiva, cornea, and anterior segment of the globe. These include allergic conjunctivitis, acne rosacea, superficial punctate keratits, herpes zoster keratitis, iritis, cyclitis, selected infective conjunctivities when the inherent hazard of steroid use is accepted to obtain an advisable diminution in edema and inflammation; corneal injury from chemical or thermal burns, or penetration of foreign bodies.

CONTRAININDICATIONS

Contraindicated in epithelial herpes simplex keratitis (dendritic keratitis); fungal diseases of ocular structures; acute infectious stages of vaccinia, varicella and many other viral disease of the cornea and conjunctiva; mycobacterial infection of the eye and in those persons who have shown hypersensitivity to any component of this preparation.

WARNINGS

Prolonged use may result in ocular hypertension and/or glaucoma, with damage to the optic nerve, defects in visual acuity and fields of vision, and posterior subcapsular cataract formation. Prolonged use may suppress the host response an thus increase the hazard of secondary ocular infections. In those diseases causing thinning of the cornea or sclera, perforations have been known to occur with the use of topical corticosteroids. In acute purulent conditions of the eye, corticosteroids may mask infection or enhance existing infection. If these products are used for 10 days or longer, intraocular pressure should be routinely monitored even though it may be difficult in children and uncooperative patients. Employment of corticosteroid medication in the treatment of herpes simplex other than epithelial herpes simplex keratitis, in which it is contraindicated, requires great caution; periodic slit-lamp microscopy is essential.

PRECAUTIONS

General

The possibility of persistent fungal infections of the cornea should be considered after prolonged corticosteroid dosing.

Information for Patients

Do not touch tube tip to any surface, as this may contaminate the contents.

Carcinogenesis, Mutagenesis, Impairment of Fertility

Long-term animal studies have not been performed to evaluate the carcinogenic potential or the effect on fertility of MAXIDEX® Ointment.

Pregnancy

Pregnancy Category C. Dexamethasone has been shown to be teratogenic in mice and rabbits following topical ophthalmic application in multiples of the therapeutic dose.

In the mouse, corticosteroids produce fetal resorptions and a specific abnormality, cleft palate. In the rabbit, corticosteroids have produced fetal resorptions and multiple abnormalities involving the head, ears, limbs, palate, etc.

There are no adequate or well-controlled studies in pregnant women. MAXIDEX Ointment should be used during pregnancy only if the potential benefit to the mother justifies the potential risk to the embryo or fetus. Infants born of mothers who have received substantial doses of corticosteroids during pregnancy should be observed carefully for signs of hypoadrenalism.

Nursing Mothers

Topically applied steroids are absorbed systemically. Therefore, because of the potential for serious adverse reactions in nursing infants from dexamethasone sodium phosphate, a decision should be made whether to discontinue nursing or discontinue the drug, taking into account the importance of the drug to the mother.

Pediatric Use

Safety and effectiveness in children have not been established.

ADVERSE REACTIONS

The following adverse reactions have been reported: glaucoma with optic nerve damage, visual acuity and field defects, posterior subcapsular cataract formation, secondary ocular infections from pathogens including herpes simplex, and perforation of the globe. Rarely, filtering blebs have been reported when topical steroids have been used following cataract surgery. Rarely, stinging or burning may occur.

DOSAGE AND ADMINSTRATION

The duration of treatment will vary with the type of lesion and may extend from a few days to several weeks, according to therapeutic response. Relapses, more common in chronic active lesions than in self-limited conditions, usually respond to treatment. Apply a one-half to one inch ribbon of ointment into the conjunctival sac(s) up to four times daily. When a favorable response is observed, dosage may be reduced gradually to once a day application for several days. MAXIDEX Ointment may be used in conjunction with MAXIDEX suspension.

HOW TO APPLY MAXIDEX OINTMENT

1. Tilt your head back.
2. Place a finger on your cheek just under your eye and gently pull down until a “V” pocket is formed between your eyeball and your lower lid.
3. Place a small amount (about ½ inch) of MAXIDEX in the “V” pocket. Do not let the tip of the tube touch your eye.
4. Look downward before closing your eye.

HOW SUPPLIED

In 3.5g ophthalmic tubes.

NDC 0065-0616-35

STORAGE

Store at 8° - 27°C (46° to 80°F).

CAUTION: Federal (USA) law prohibits dispensing without prescription.

ALCON®

Ophthalmic

Alcon Laboratories, Inc.

Fort Worth, Texas 76134